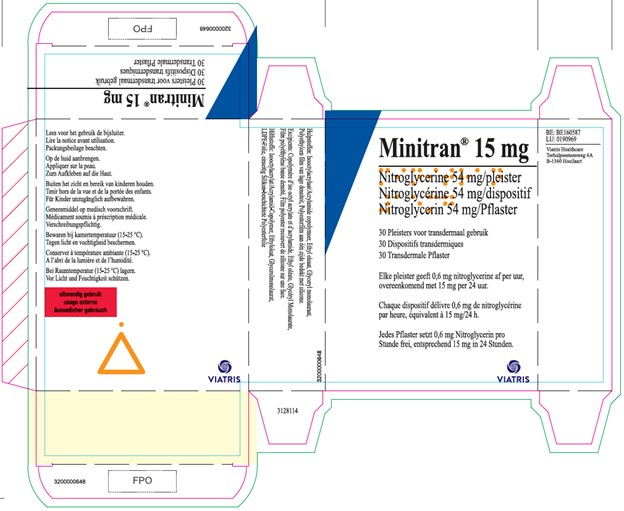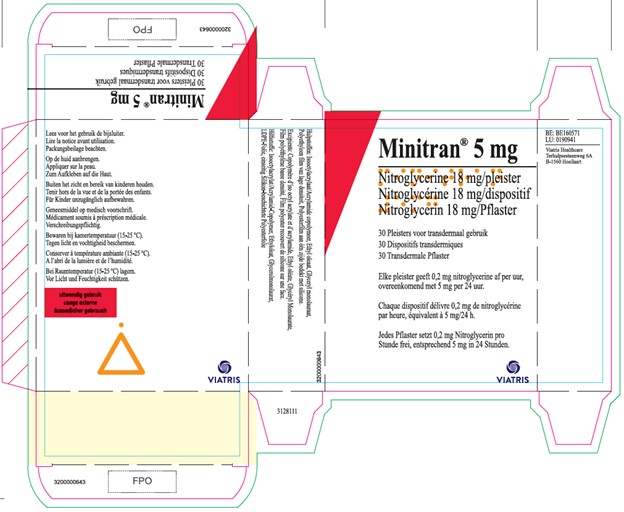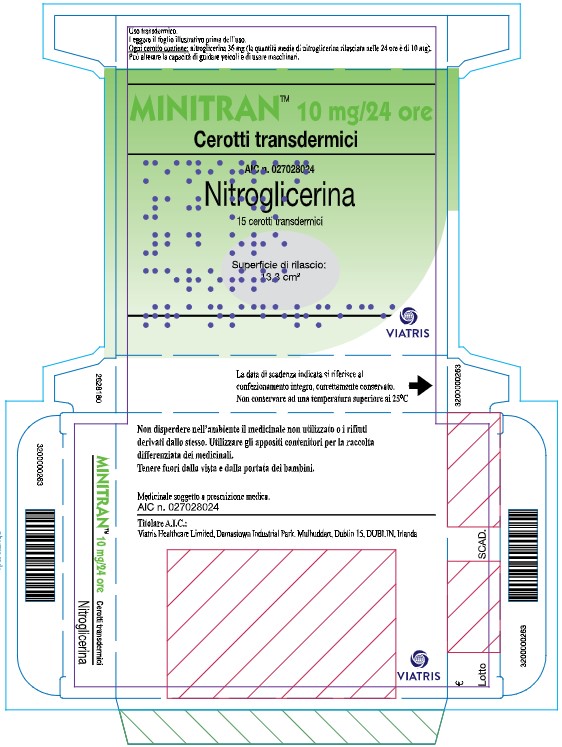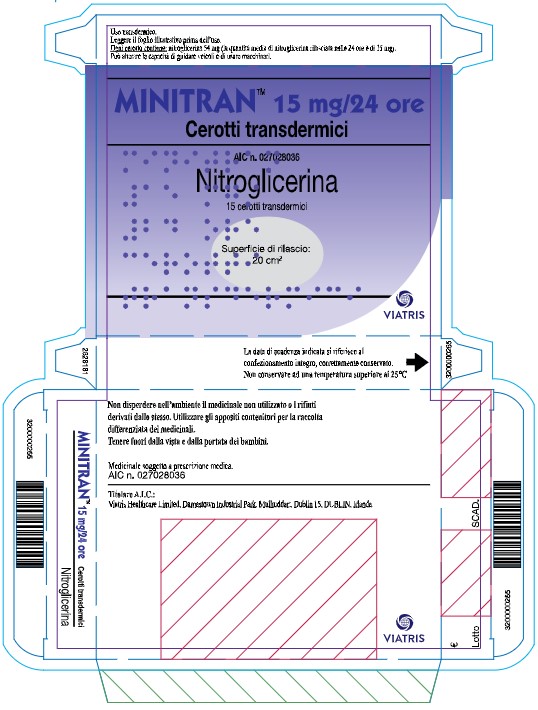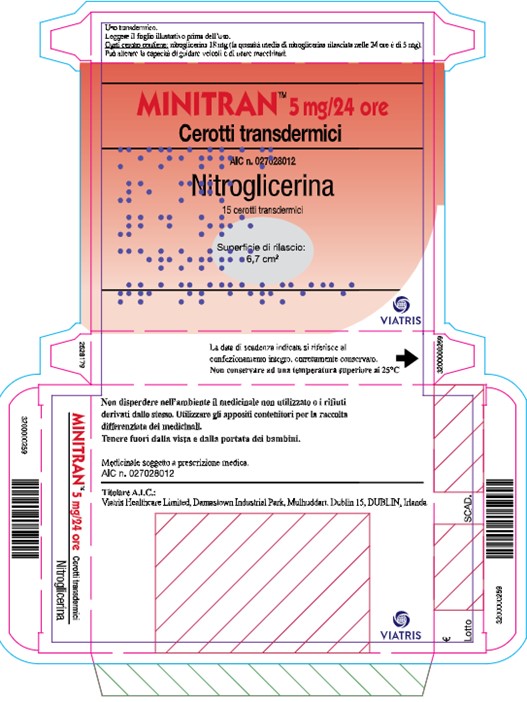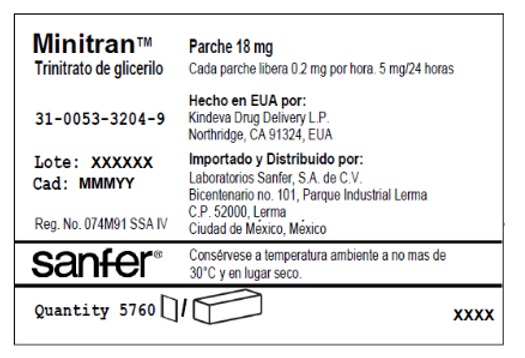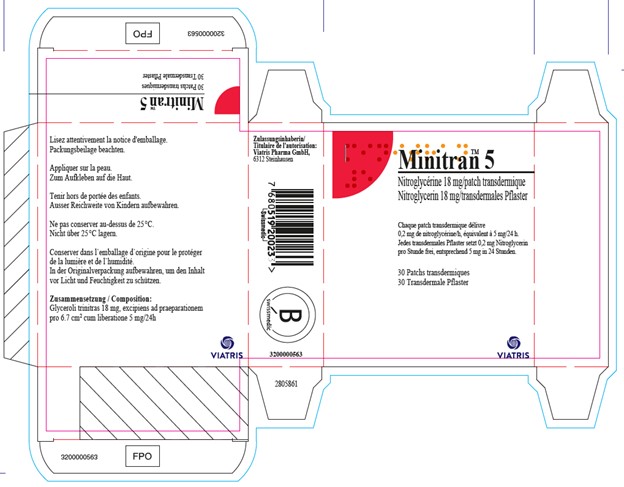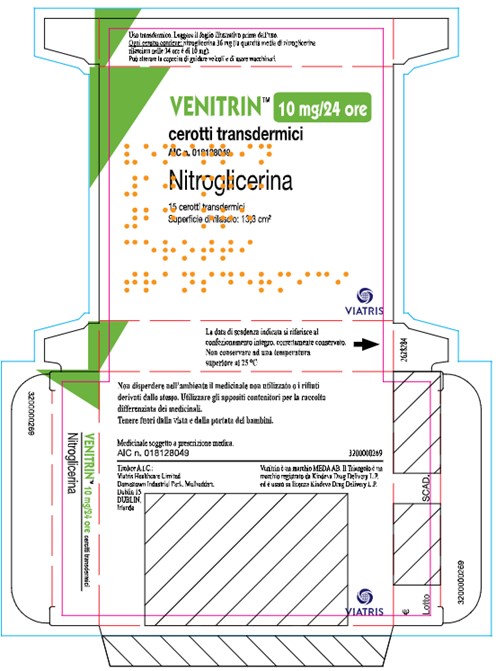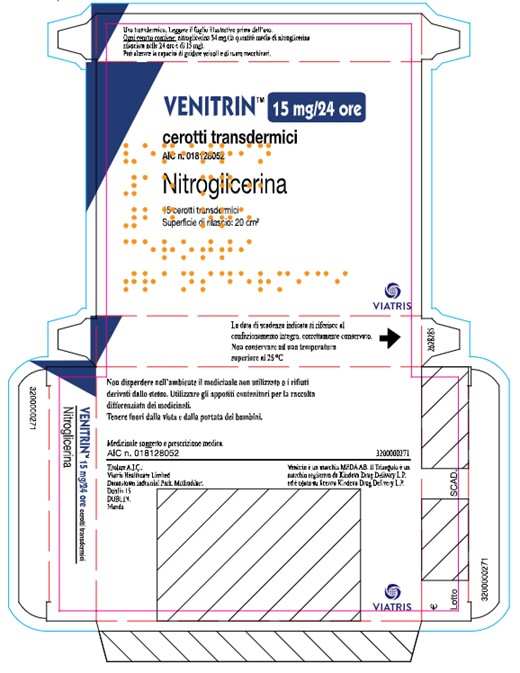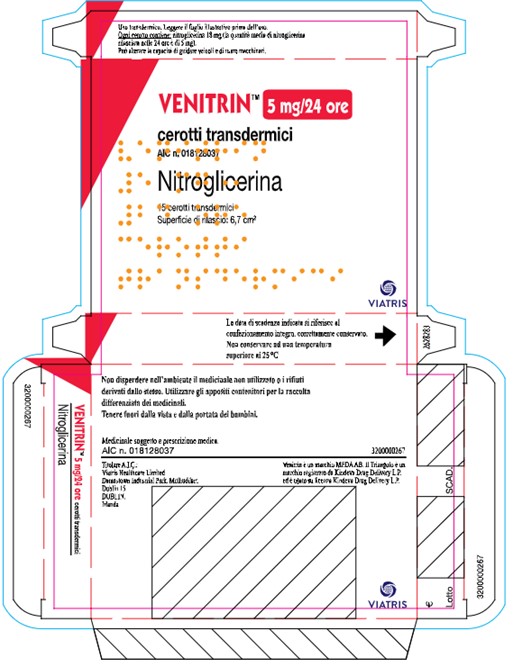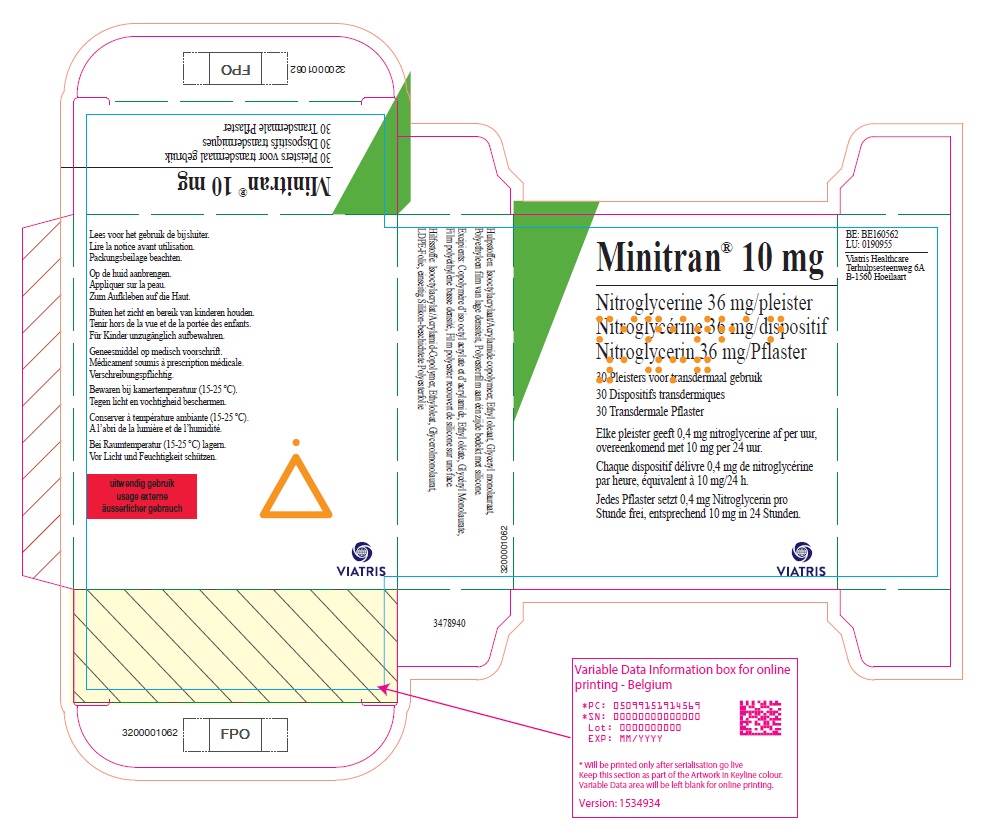 DRUG LABEL: Minitran
NDC: 0089-0171 | Form: PATCH
Manufacturer: Kindeva Drug Delivery L.P.
Category: prescription | Type: HUMAN PRESCRIPTION DRUG LABEL
Date: 20251201

ACTIVE INGREDIENTS: NITROGLYCERIN 18 mg/1 1

MINITRAN (nitroglycerin) - EXPORT ONLY

MINITRAN™ 5 mg (Italy)

MINITRAN™ 5 mg/24 ore

Cerotti transdermici

AIC n. 027028012

Nitroglicerina

15 cerotti transdermici

Superficie di rilascio:

6,7 cm^2

VIATRIS

VENITRIN™ 5 mg (Italy)

VENITRIN™ 5 mg/24 ore

cerotti transdermici

Alc n. 018128037

Nitroglicerina

15 cerotti transdermici

Superficie di rilascio: 6,7 cm^2

VIATRIS

Minitran™ 5 mg (Switzerland)

Minitran™ 5 mg

Nitroglycérine 18mg/patch transdermique

Nitroglycerin 18 mg/transdermales Pflaster

Chaque patch transdermique délivre

0,2 mg de nitroglycérine/h, équivalent à 5 mg/24 h.

Jedes transdermales Pflaster setzt 0,2 mg Nitroglycerin

pro Stunde frei, entsprechend 5 mg in 24 Stunden.

30 Patchs transdermiques

30 Transdermale Pflaster

VIATRIS

Minitran® 5 mg (Belgium)

Minitran® 5 mg

Nitroglycerine 18 mg/pleister

Nitroglycérine 18 mg/dispositif

Nitroglycerin 18 mg/Pflaster

30 Pleisters voor transdermaal gebruik

30 Dispositifs transdermiques

30 Transdermale Pflaster

Elke pleister geeft 0,2 mg nitroglycerine af per uur,

overeenkomend met 5 mg per 24 uur.

Chaque dispositif délivre 0,2 mg de nitroglycérine

par heure, équivalent à 5 mg/24 h.

Jedes Pflaster setzt 0,2 mg Nitroglycerin pro

Stunde frei, entsprechend 5 mg in 24 Stunden.

VIATRIS

Minitran™ 5 mg (Mexico)

Minitran™

Trinitrato de glicerilo

31-0053-3204-9

Lote: XXXXXX

Cad: MMMYY

Reg. No. 074M91 SSA IV

Parche 18 mg

Cada parche libera 0.2 mg por hora. 5 mg/24 horas

Hecheo en EUA por:

Kindeva Drug Delivery L.P.

Northridge, CA 91324, EUA

Importado y Distribuido por:

Laboratorios Sanfer, S.A. de C.V.

Bicentenario no. 101, Parque Industrial Lerma

C.P. 52000, Lerma

Ciudad de México, México

sanfer®

Consérvese a temperatura ambiente a no mas de

30°C y en lugar seco.

Quantity 5760

MINITRAN™ 10 mg (Italy)

MINITRAN™ 10 mg/24 ore

Cerotti transdermici

AIC n. 027028024

Nitroglicerina

15 cerotti transdermici

Superficie di rilascio:

13,3 cm^2

VIATRIS

VENITRIN™ 10 mg (Italy)

VENITRIN™ 10mg/24 ore

cerotti transdermici

AIC n. 018128049

Nitroglicerina

15 cerotti transdermici

Superficie di rilascio: 13,3 cm^2

VIATRIS

Minitran® 10 mg (Belgium)

Minitran® 10 mg

Nitroglycerine 36 mg/pleister

Nitroglycérine 36 mg/dispositif

Nitroglycerin 36 mg/Pflaster

30 Pleisters voor transdermaal gebruik

30 Dispositifs transdermiques

30 Transdermale Pflaster

Elke pleister geeft 0,4 mg nitroglycerine af per uur,

overeenkomend met 10 mg per 24 uur.

Chaque dispositif délivre 0,4 mg de nitroglycérine

par heure, équivalent à 10 mg/24 h.

Jedes Pflaster setzt 0,4 mg Nitroglycerin pro

Stunde frei, entsprechend 10 mg in 24 Stunden.

VIATRIS

MINITRAN™ 15 mg (Italy)

MINITRAN™ 15 mg/24 ore

Cerotti transdermici

AIC n. 027028036

Nitroglicerina

15 cerotti transdermici

Superficie di rilascio:

20 cm^2

VIATRIS

VENITRIN™ 15 mg (Italy)

VENITRIN™ 15 mg/24 ore

cerotti transdermici

AlC n. 018128052

Nitroglicerina

15 cerotti transdermici

Superficie di rilascio: 20 cm^2

VIATRIS

Minitran® 15 mg (Belgium)

Minitran® 15 mg

Nitroglycerine 54 mg/pleister

Nitroglycérine 54 mg/dispositif

Nitroglycerin 54 mg/Pflaster

30 Pleisters voor transdermaal gebruik

30 Dispositifs transdermiques

30 Transdermale Pflaster

Elke pleister geeft 0,6 mg nitroglycerine af per uur,

overeenkomend met 15 mg per 24 uur.

Chaque dispositif délivre 0,6 mg de nitroglycérine

par heure, équivalent à 15 mg/24 h.

Jedes Pflaster setzt 0,6 mg Nitroglycerin pro

Stunde frei, entsprechend 15 mg in 24 Stunden.

VIATRIS